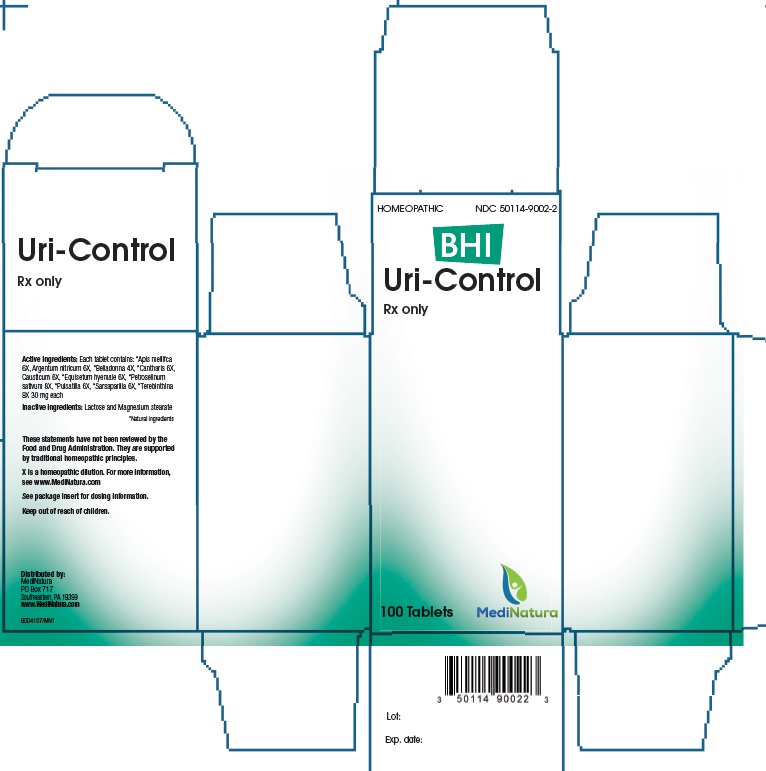 DRUG LABEL: BHI Uri-Control RX
NDC: 50114-9002 | Form: TABLET
Manufacturer: MediNatura Inc
Category: homeopathic | Type: HUMAN PRESCRIPTION DRUG LABEL
Date: 20211018

ACTIVE INGREDIENTS: APIS MELLIFERA 6 [hp_X]/1 1; SILVER NITRATE 6 [hp_X]/1 1; ATROPA BELLADONNA 4 [hp_X]/1 1; LYTTA VESICATORIA 6 [hp_X]/1 1; CAUSTICUM 8 [hp_X]/1 1; EQUISETUM HYEMALE 6 [hp_X]/1 1; PETROSELINUM CRISPUM 8 [hp_X]/1 1; PULSATILLA VULGARIS 6 [hp_X]/1 1; SMILAX ORNATA ROOT 6 [hp_X]/1 1; TURPENTINE OIL 8 [hp_X]/1 1
INACTIVE INGREDIENTS: LACTOSE; MAGNESIUM STEARATE

BHI Uri-Control RX Tablet

DESCRIPTION

Ingredient name | Potency | Quantity | Final dilution
Apis mellifica | 6X | 30 mg | 7X
Argentum nitricum | 6X | 30 mg | 7X
Belladonna | 4X | 30 mg | 5X
Cantharis | 6X | 30 mg | 7X
Causticum | 8X | 30 mg | 5X
Equisetum hyemale | 6X | 30 mg | 7X
Petroselinum sativum | 8X | 30 mg | 9X
Pulsatilla | 6X | 30 mg | 7X
Sarsaparilla | 6X | 30 mg | 7X
Terebinthina | 8X | 30 mg | 9X

INDICATIONS & USAGE

Uri-Control is a homeopathic drug indicated for the treatment of urinary tract infection, albuminuria, hematuria, incontinence.

DOSAGE AND ADMINISTRATION

Allow tablets to dissolve completely in the mouth, do not swallow.

• Standard Dosage:

Adults and children 12 years and older: 3 tablets per day, taking 1 tablet every 4 to 6 hours. Children under 12 years: 2 tablets per day, taking 1 tablet every 6 to 8 hours.

• Acute Dosage:

Adults and children 12 years and older: 1 tablet every ½ to 1 hour until symptoms lessen, then continue with standard dosage. Do not exceed 12 tablets in 24 hours. Children under 12 years: 1 tablet every ½ to 1 hour until symptoms lessen, then continue with standard dosage. Do not exceed 8 tablets in 24 hours.

WARNINGS

Keep out of reach of children.

DOSAGE

300 mg tablets each containing the active ingredients in the strengths listed under Description.